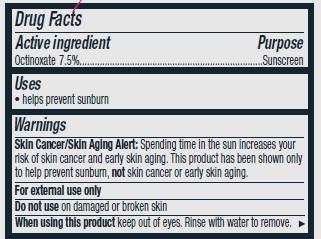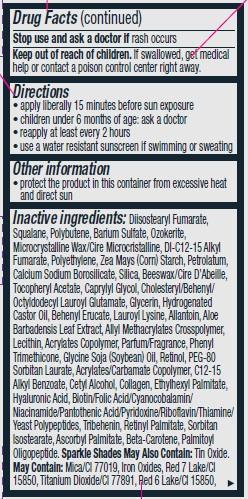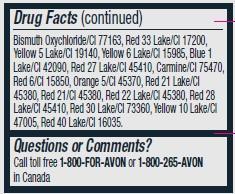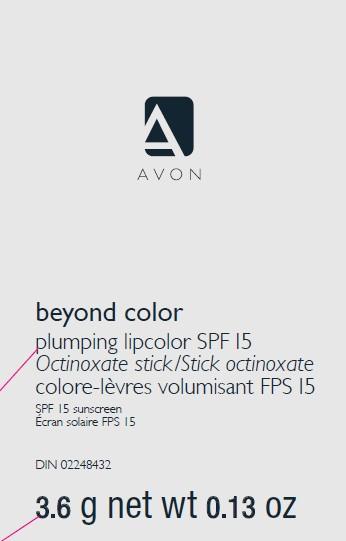 DRUG LABEL: Beyond Color
NDC: 10096-0038 | Form: LIPSTICK
Manufacturer: Avon Products, Inc
Category: otc | Type: HUMAN OTC DRUG LABEL
Date: 20130209

ACTIVE INGREDIENTS: OCTINOXATE 75 mg/1 g

Active ingredient
Octinoxate 7.5%................................

Purpose
...............................Sunscreen

Uses
• helps prevent sunburn

Warnings
Skin Cancer/Skin Aging Alert: Spending time in the sun increases your risk of skin cancer and early skin aging. This product has been shown only to help prevent sunburn, not skin cancer or early skin aging.
For external use only

Do not use on damaged or broken skin

When using this product keep out of eyes. Rinse with water to remove.

Stop use and ask a doctor if rash occurs

Keep out of reach of children. If swallowed, get medical help or contact a poison control center right away.

Directions
• apply liberally 15 minutes before sun exposure
• children under 6 months of age: ask a doctor
• reapply at least every 2 hours
• use a water resistant sunscreen if swimming or sweating

Other information
• protect the product in this container from excessive heat and direct sun

INACTIVE INGREDIENT

Inactive ingredients:Diisostearyl Fumarate, Squalane, Polybutene, Barium Sulfate, Ozokerite, Microcrystalline Wax/Cire Microcristalline, DI-C12-15 Alkyl Fumarate, Polyethylene, Zea Mays (Corn) Starch, Petrolatum, Calcium Sodium Borosilicate, Silica, Beeswax/Cire D’Abeille,
Tocopheryl Acetate, Caprylyl Glycol, Cholesteryl/Behenyl/Octyldodecyl Lauroyl Glutamate, Glycerin, Hydrogenated Castor Oil, Behenyl Erucate, Lauroyl Lysine, Allantoin, Aloe Barbadensis Leaf Extract, Allyl Methacrylates Crosspolymer, Lecithin, Acrylates Copolymer, Parfum/Fragrance, Phenyl Trimethicone, Glycine Soja (Soybean) Oil, Retinol, PEG-80 Sorbitan Laurate, Acrylates/Carbamate Copolymer, C12-15 Alkyl Benzoate, Cetyl Alcohol, Collagen, Ethylhexyl Palmitate, Hyaluronic Acid, Biotin/Folic Acid/Cyanocobalamin/Niacinamide/Pantothenic Acid/Pyridoxine/Riboflavin/Thiamine/Yeast Polypeptides, Tribehenin, Retinyl Palmitate, Sorbitan Isostearate, Ascorbyl Palmitate, Beta-Carotene, Palmitoyl Oligopeptide. Sparkle Shades May Also Contain: Tin Oxide. May Contain: Mica/CI 77019, Iron Oxides, Red 7 Lake/CI 15850, Titanium Dioxide/CI 77891, Red 6 Lake/CI 15850, Bismuth Oxychloride/CI 77163, Red 33 Lake/CI 17200, Yellow 5 Lake/CI 19140, Yellow 6 Lake/CI 15985, Blue 1 Lake/CI 42090, Red 27 Lake/CI 45410, Carmine/CI 75470, Red 6/CI 15850, Orange 5/CI 45370, Red 21 Lake/CI 45380, Red 21/CI 45380, Red 22 Lake/CI 45380, Red 28 Lake/CI 45410, Red 30 Lake/CI 73360, Yellow 10 Lake/CI 47005, Red 40 Lake/CI 16035.

Questions or Comments?
Call toll free 1-800-FOR-AVON or 1-800-265-AVON
in Canada